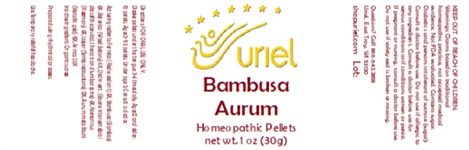 DRUG LABEL: Bambusa Aurum
NDC: 48951-2009 | Form: PELLET
Manufacturer: Uriel Pharmacy Inc.
Category: homeopathic | Type: HUMAN OTC DRUG LABEL
Date: 20250627

ACTIVE INGREDIENTS: FORMICA RUFA 5 [hp_X]/1 1; BAMBUSA VULGARIS WHOLE 6 [hp_X]/1 1; STACHYS OFFICINALIS 6 [hp_X]/1 1; BOS TAURUS INTERVERTEBRAL DISC 6 [hp_X]/1 1; ROSMARINUS OFFICINALIS FLOWERING TOP 6 [hp_X]/1 1; SILICON DIOXIDE 12 [hp_X]/1 1; GOLD 16 [hp_X]/1 1; ARNICA MONTANA 20 [hp_X]/1 1
INACTIVE INGREDIENTS: SUCROSE

Bambusa Aurum

INDICATIONS AND USAGE

Directions: FOR ORAL USE ONLY.

DOSAGE AND ADMINISTRATION

Dissolve pellets under the tongue 3-4 times daily. Ages 12 and older: 10 pellets. Ages 2-11: 5 pellets. Under age 2: Consult a doctor.

ACTIVE INGREDIENT

Active Ingredients: Formica (Red wood ant) 5X, Bambusa (Bamboo) 6X, Betonica (Wood betony) 6X, Disci invert. (Bovine intervertebral discs of the cervical, thoracic and lumbar spine) 6X, Rosmarinus (Rosemary) 6X, Jasper (Semiprecious stone) 12X, Aurum metallicum (Metallic gold) 15X, Arnica 20X

Inactive Ingredient: Organic sucrose

Prepared using rhythmical processes.

PURPOSE

Use: Temporary relief of headache.

KEEP OUT OF REACH OF CHILDREN.

WARNINGS

Warnings: Claims based on traditional homeopathic practice, not accepted medical evidence. Not FDA evaluated. Contains sugar. Diabetics and persons intolerant of sucrose (sugar): Consult a doctor before use. Do not use if allergic to any ingredient. Consult a doctor before use for serious conditions or if conditions worsen or persist. If pregnant or nursing, consult a doctor before use. Do not use if safety seal is broken or missing.

QUESTIONS

Questions? Call 866.642.2858 Uriel, East Troy, WI 53120 shopuriel.com

Lot: